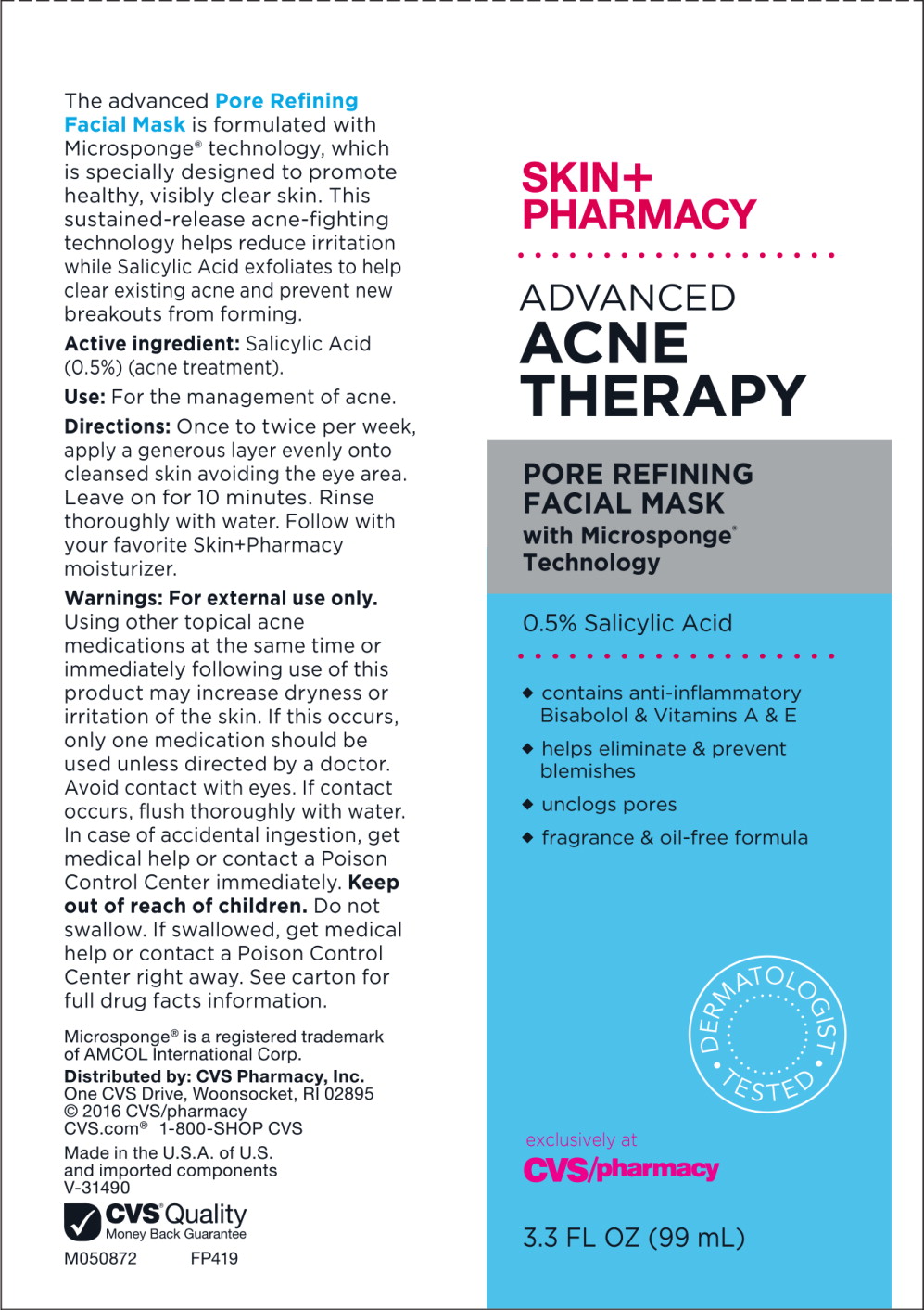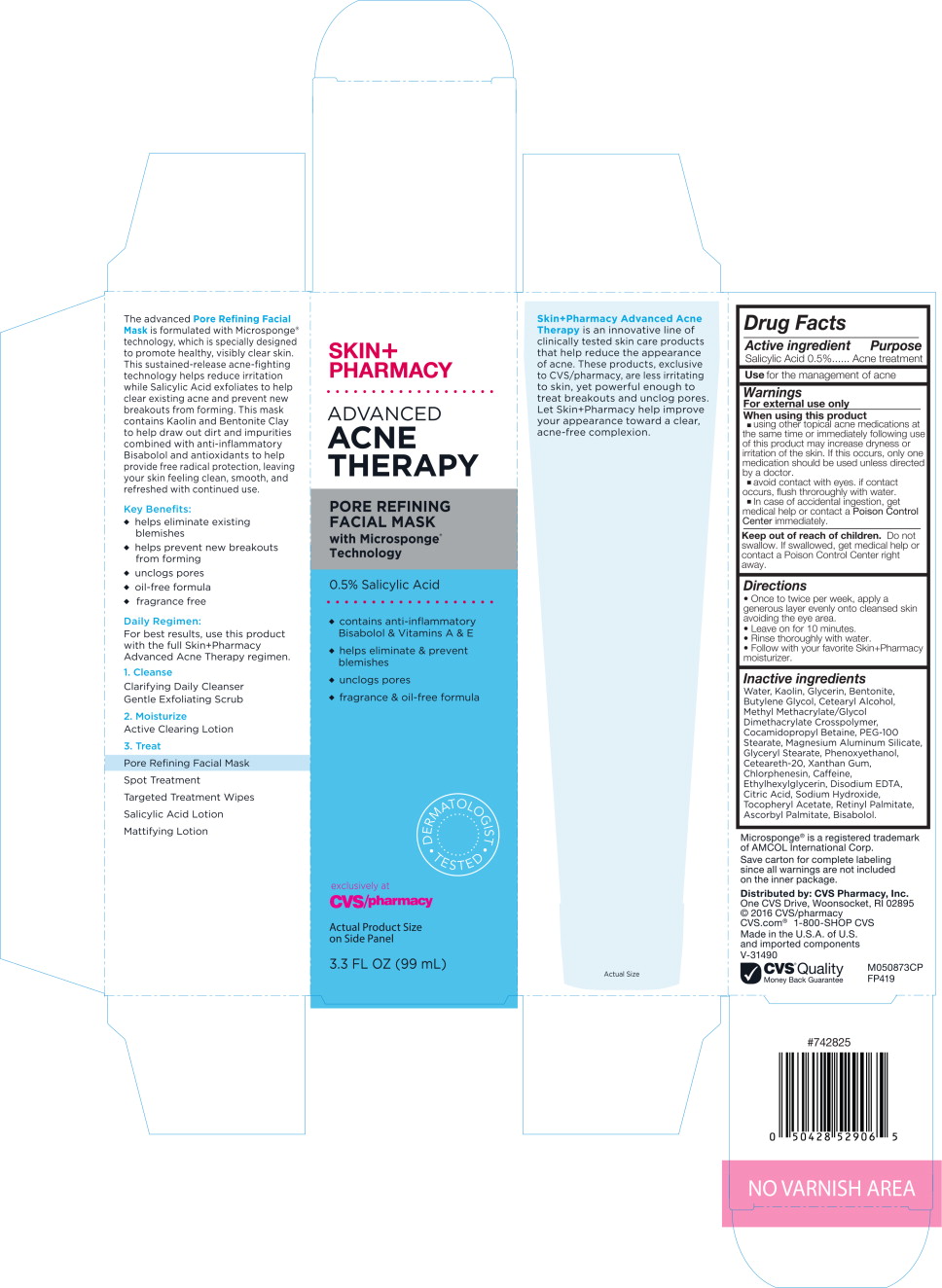 DRUG LABEL: SKINPHARMACY ADVANCED ACNE THERAPY PORE REFINING FACIAL MASK
NDC: 69842-077 | Form: LIQUID
Manufacturer: CVS Health
Category: otc | Type: HUMAN OTC DRUG LABEL
Date: 20170314

ACTIVE INGREDIENTS: salicylic acid 5 mg/1 mL
INACTIVE INGREDIENTS: water; kaolin; glycerin; bentonite; butylene glycol; cetostearyl alcohol; methyl methacrylate/glycol dimethacrylate crosspolymer; cocamidopropyl betaine; peg-100 stearate; magnesium aluminum silicate; glyceryl monostearate; phenoxyethanol; polyoxyl 20 cetostearyl ether; xanthan gum; chlorphenesin; caffeine; ethylhexylglycerin; edetate disodium; citric acid monohydrate; sodium hydroxide; .alpha.-tocopherol acetate; vitamin a palmitate; ascorbyl palmitate; levomenol

Drug Facts

Active Ingredient

Salicylic Acid 0.5%

Purpose

Acne

Use

for the management of acne

Warnings

For external use only

When using this product

- using other topical acne medications at the same time or immediately following use of this product may increase dryness or irritation of the skin. If this occurs, only one medication should be used unless directed by a doctor.
- avoid contact with eye. if contact occurs, flush thoroughly with water.
- In case of accidental ingestion, get medical help or contact a Poison Control Center immediately.

Keep out of reach of children. Do not swallow. If swallowed, get medical help or contact a Poison Control Center right away.

Directions

- Once to twice per week, apply a generous layer evenly onto cleansed skin avoiding the eye area.
- Leave on for 10 minutes.
- Rinse thoroughly with water.
- Follow with your favorite Skin+Pharmacy moisturizer.

Inactive ingredients

Water, Kaolin, Glycerin, Bentonite, Butylene Glycol, Cetearyl Alcohol, Methyl Methacrylate/Glycol Dimethacrylate Crosspolymer, Cocamidopropyl Betaine, PEG-100 Stearate, Magnesium Aluminum Silicate, Glyceryl Stearate, Phenoxyethanol, Ceteareth-20, Xanthan Gum, Chlorphenesin, Caffeine, Ethylhexylglycerin, Disodium EDTA, Citric Acid, Sodium Hydroxide, Tocopheryl Acetate, Retinyl Palmitate, Ascorbyl Palmitate, Bisabolol.

Microsponge® is a registered trademark of AMCOL International Corp.

Save carton for complete labeling since all warnings are not included on the inner package.

Distributed by: CVS Pharmacy, Inc.

One CVS Drive, Woonsocket, RI 02895

© 2016 CVS/pharmacy

CVS.com® 1-800-SHOP CVS

Made in the U.S.A. of U.S. and foreign components

V-13649

CVS® Quality

Money Back Guarantee

M050873CP

FP419

#742825

Principal Display Panel - Carton Label

SKIN+
PHARMACY

ADVANCED
ACNE
THERAPY

PORE REFINING
FACIAL MASK
with Microsponge®
Technology

0.5% Salicylic Acid

- contains anti-inflammatory Bisabolol & Vitamins A & E
- helps eliminate & prevent blemishes
- unclogs pores
- fragrance & oil-free formula

DERMATOLOGIST TESTED

exclusively at
CVS/pharmacy

Actual Product Size
on Side Panel

3.3 FL OZ (99 mL)

Principal Display Panel - Tube Label

SKIN+
PHARMACY

ADVANCED
ACNE
THERAPY

PORE REFINING
FACIAL MASK
with Microsponge®
Technology

0.5% Salicylic Acid

- contains anti-inflammatory Bisabolol & Vitamins A & E
- helps eliminate & prevent blemishes
- unclogs pores
- fragrance & oil-free formula

DERMATOLOGIST TESTED

exclusively at
CVS/pharmacy

3.3 FL OZ (99 mL)